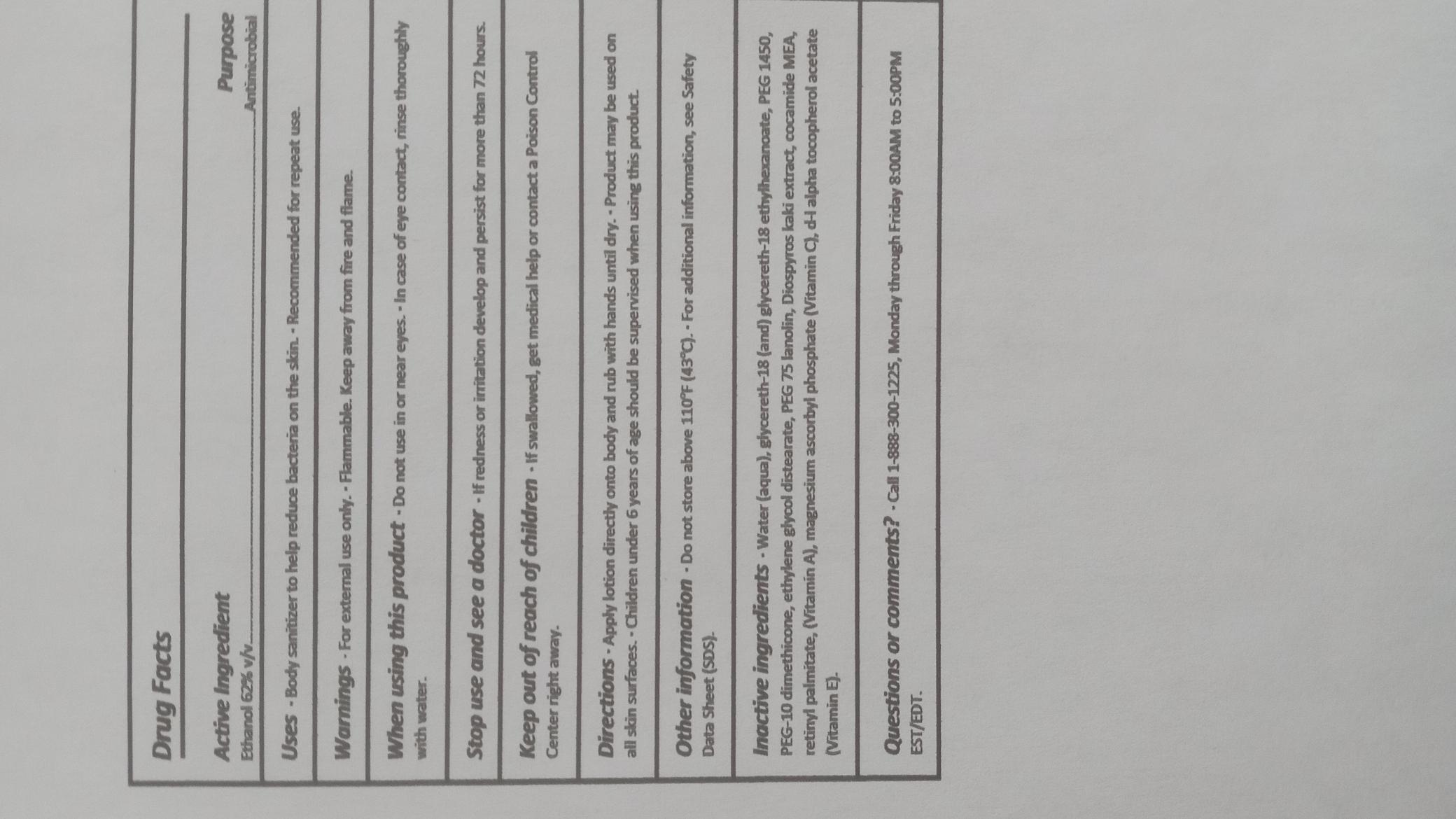 DRUG LABEL: Mist
NDC: 70741-003 | Form: SPRAY
Manufacturer: Derma Glove
Category: otc | Type: HUMAN OTC DRUG LABEL
Date: 20251114

ACTIVE INGREDIENTS: Alcohol 62 mL/100 mL
INACTIVE INGREDIENTS: Water 30 mL/100 mL

ACTIVE INGREDIENT

Ethanol 62% v/v

PURPOSE

Antimicrobial

WARNINGS

For external use only. Flammable. Keep away from children.

Do not use in or near eyes. In case of eye contact, rinse thoroughly with water.

STOP USE

If redness or irritation develop and persist for more than 72 hours.

KEEP OUT OF REACH OF CHILDREN

If swallowed, get medical help or contact a Poison Control Center right away.

INDICATIONS AND USAGE

Apply lotion directly onto body and rub with hands until dry. Product may be used on all skin surfaces. Children under 6 years of age should be supervised when using this product.

DOSAGE AND ADMINISTRATION

Apply lotion directly onto body and rub with hands until dry. Product may be used on all skin surfaces. Children under 6 years of age should be supervised when using this product.

OTHER SAFETY INFORMATION

Do not store above 110oF (43oC). For additional information, see Safety Data Sheet (SDS).

INACTIVE INGREDIENT

Water (aqua), glycereth-18 (and) glycereth-18 ethylhexanoate, PEG 1450, PEG-10 dimethicone, cocamide MEA, ethylene glycol distearate, PEG 75 lanolin, Diospyros kaki extract, retinyl palmitate (Vitamin A), magnesium ascorbyl phosphate (Vitamin C), d-l alpha tocopherol acetate (Vitamin E).

QUESTIONS

Call 1-888-300-1225, Monday through Friday 8:00AM to 5:00PM EST/EDT.